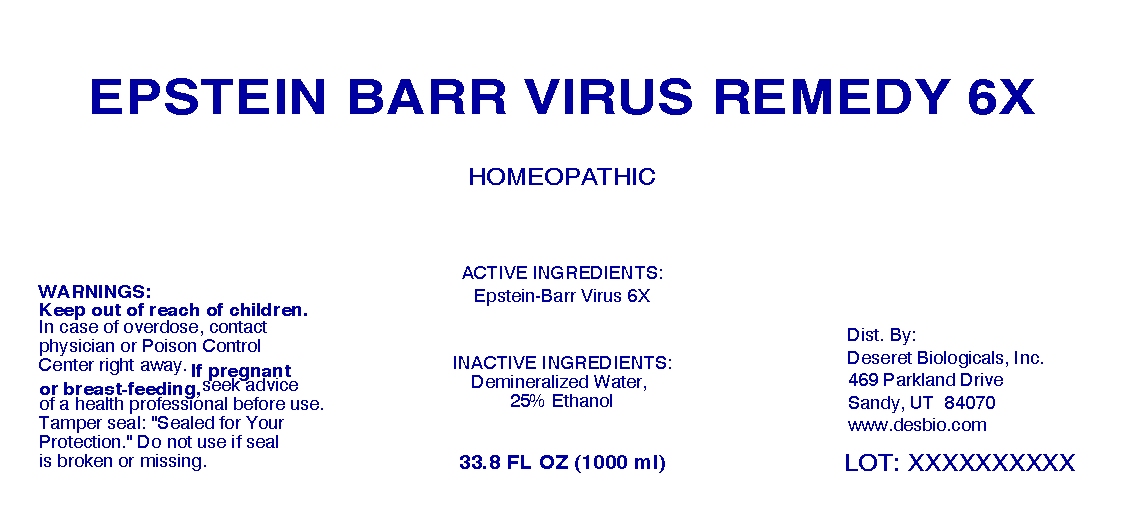 DRUG LABEL: Epstein Barr Virus Remedy
NDC: 57520-0174 | Form: LIQUID
Manufacturer: Apotheca Company
Category: homeopathic | Type: HUMAN OTC DRUG LABEL
Date: 20100517

ACTIVE INGREDIENTS: HUMAN HERPESVIRUS 4 6 [hp_X]/1 mL
INACTIVE INGREDIENTS: WATER; ALCOHOL

Epstein Barr Virus Remedy 6X

ACTIVE INGREDIENTS: Epstein-Barr Virus 6X

WARNINGS

WARNINGS: Keep out of reach of children. In case of overdose, contact physician or Poison Control Center right away.

If pregnant or breast-feeding, seek advice of a health professional before use.

Tamper seal: "Sealed for your protection." Do not use if seal is broken or missing.

INACTIVE INGREDIENTS: Demineralized Water, 25% Ethanol

PATIENT COUNSELING INFORMATION

Dist. By:

Deseret Biologicals, Inc.

469 Parkland Drive

Sandy, UT 84070

www.desbio.com

PACKAGE LABEL

EPSTEIN BARR VIRUS REMEDY 6X

HOMEOPATHIC

33.8 FL OZ (1000 ML)